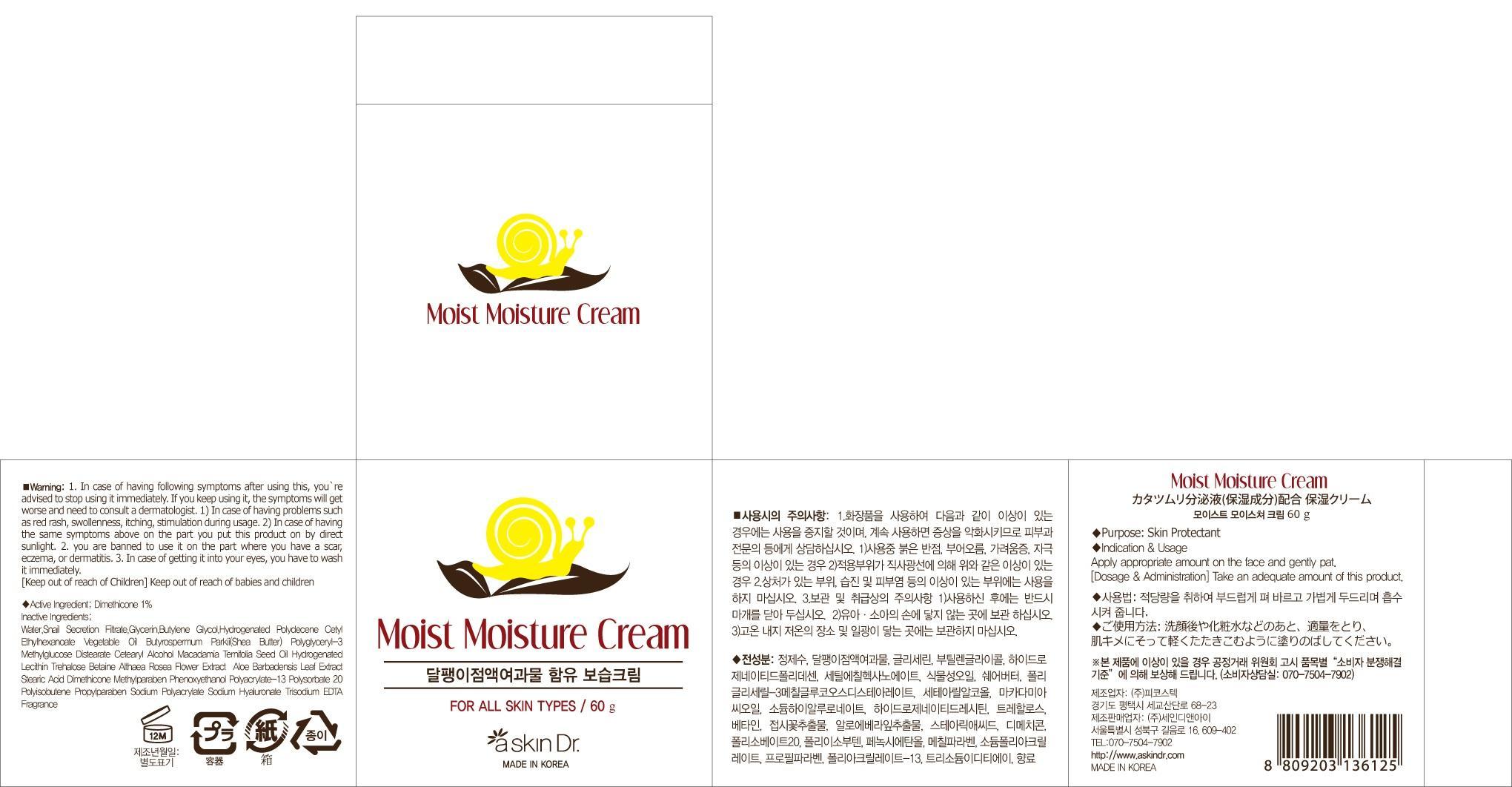 DRUG LABEL: askinDr MOIST MOISTURE
NDC: 69072-070 | Form: CREAM
Manufacturer: Seindni Co.,ltd
Category: otc | Type: HUMAN OTC DRUG LABEL
Date: 20181210

ACTIVE INGREDIENTS: Dimethicone 0.60 mg/60 g
INACTIVE INGREDIENTS: Water; Glycerin

ACTIVE INGREDIENT

Active Ingredients: Dimethicone 1%

INACTIVE INGREDIENT

Inactive Ingredients:
Water, Snail Secretion Filtrate, Glycerin, Butylene Glycol, Hydrogenated Polydecene Cetyl Ethylhexanoate Vegetable Oil Butyrospermum Parkii(Shea Butter) Polyglyceryl-3 Methylglucose Distearate Cetearyl Alcohol Macadamia Ternifolia Seed Oil Hydrogenated Lecithin Trehalose Betaine Althaea Rosea Flower Extract Aloe Barbadensis Leaf Extract Stearic Acid Dimethicone Methylparaben Phenoxyethanol Polyacrylate-13 Polysorbate 20 Polyisobutene Propylparaben Sodium Polyacrylate Sodium Hyaluronate Trisodium EDTA Fragrance

PURPOSE

Purpose: Skin Protectant

WARNINGS

Warning:
1. In case of having following symptoms after using this, you're advised to stop using it immediately. If you keep using it, the symptoms will get worse and need to consult a dermatologist. 1) In case of having problems such as red rash, swollenness, itching, stimulation during usage. 2) In case of having the same symptoms above on the part you put this product on by direct sunlight. 2. you are banned to use it on the part where you have a scar, eczema, or dermatitis. 3. In case of getting it into your eyes, you have to wash it immediately.

Keep out of reach of children: Keep out of reach of babies and children

INDICATIONS AND USAGE

Indication and Usage: Apply appropriate amount on the face and gently pat.

Dosage and Administration: Take an adequate amount of this product.